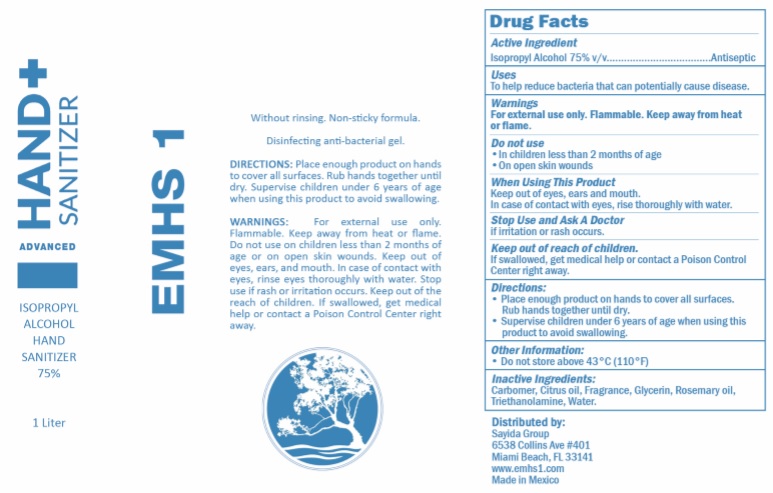 DRUG LABEL: EMHS 1 Hand Sanitizer
NDC: 77858-0755 | Form: GEL
Manufacturer: Sayida Group
Category: otc | Type: HUMAN OTC DRUG LABEL
Date: 20200626

ACTIVE INGREDIENTS: ISOPROPYL ALCOHOL 75 L/100 L
INACTIVE INGREDIENTS: GLYCERIN; WATER; ROSEMARY OIL; TROLAMINE; CARBOMER 1342

EMHS1 Hand Sanitizer (1L - no pump) NDC: 77858-0755-1
EMHS1 Hand Sanitizer (1L - pump) NDC: 77858-0755-2

Active Ingredient(s)

Isopropyl Alcohol 75% v/v.

Purpose

Antiseptic

Use

To help reduce bacteria that potentially can cause disease.

Warnings

For external use only. Flammable. Keep away from heat or flame

Do not use

- in children less than 2 months of age
- on open skin wounds

When using this product keep out of eyes, ears, and mouth. In case of contact with eyes, rinse eyes thoroughly with water.

Stop use and ask a doctor if irritation or rash occurs.

Keep out of reach of children. If swallowed, get medical help or contact a Poison Control Center right away.

Directions

- Place enough product on hands to cover all surfaces. Rub hands together until dry.
- Supervise children under 6 years of age when using this product to avoid swallowing.

Other information

- Do not store above 43C (110F)

Inactive ingredients

carbomer, citrus oil, fragrance, glycerin, rosemary oil, triethanolamine, water

Side Panel

Without rinsing. Non-sticky formula. Disinfecting anti-bacterial gel.

DIRECTIONS: Place enough product on hands to cover all surfaces. Rub hands together until dry. Supervise children under 6 years of age when using this product to avoid swallowing.

WARNINGS: For external use only. Flammable. Keep away from heat or flame. Do not use on children less than 2 months of age or on open skin wounds. Keep out of eyes, ears, and mouth. In case of contact with eyes, rinse eyes thoroughly with water. Stop use if rash or irritation occurs. Keep out of the reach of children. If swallowed, get medical help or contact a Poison Control Center right away.

Distributed by: Sayida Group LLC

6538 Collins Ave #401

Miami Beach, FL33141

www.emhs1.com

Made In Mexico

Package Label - Principal Display Panel

Distributed by Sayida Group

6538 Collins Ave #401

Miami Beach, FL 33141

EMHS1 Hand Sanitizer (1L - no pump) NDC: 77858-0755-1

EMHS1 Hand Sanitizer (1L - pump) NDC: 77858-0755-2